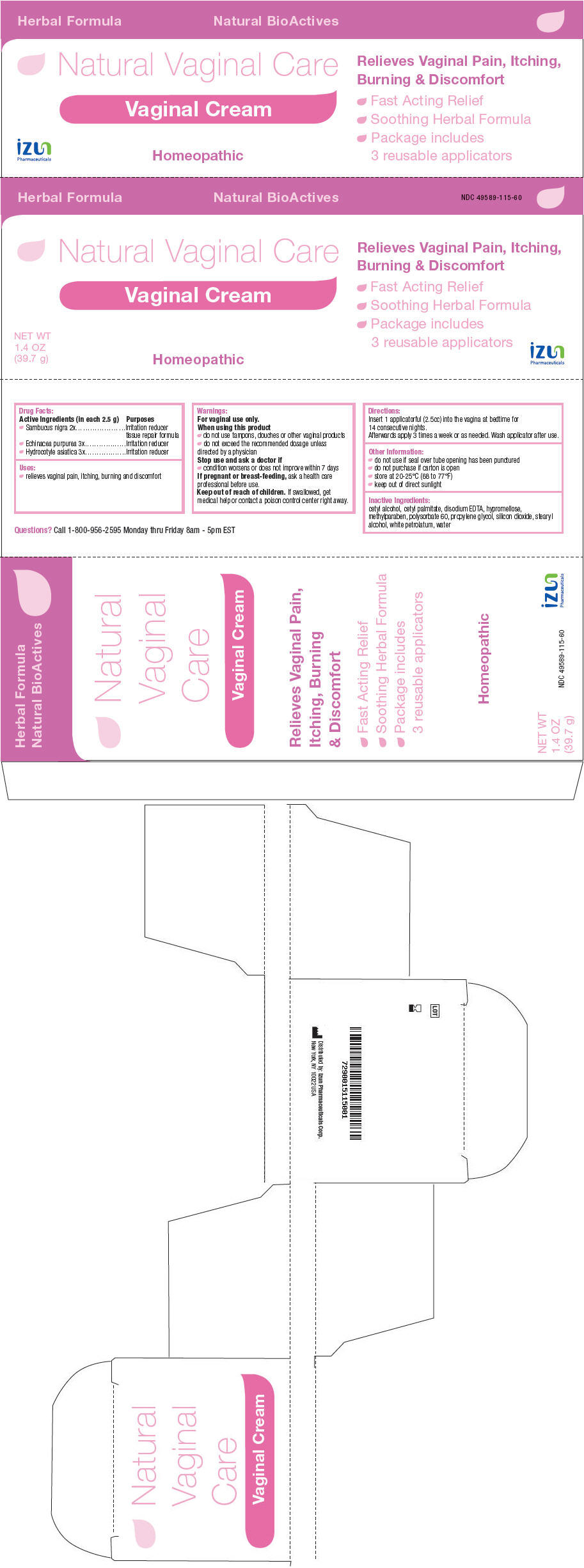 DRUG LABEL: Natural Vaginal Care
NDC: 49589-115 | Form: CREAM
Manufacturer: Izun Pharmaceuticals Corporation
Category: homeopathic | Type: HUMAN OTC DRUG LABEL
Date: 20150527

ACTIVE INGREDIENTS: Sambucus nigra flower 2 [hp_X]/2.5 g; Echinacea purpurea 3 [hp_X]/2.5 g; Centella Asiatica 3 [hp_X]/2.5 g
INACTIVE INGREDIENTS: cetyl alcohol; cetyl palmitate; edetate disodium; hypromellose 2208 (15000 mpa.s); methylparaben; polysorbate 60; propylene glycol; silicon dioxide; stearyl alcohol; petrolatum; water

Natural Vaginal Care

Drug Facts

ACTIVE INGREDIENT

PURPOSE

Active Ingredients (in each 2.5 g) | Purposes
• Sambucus nigra 2x | Irritation reducer tissue repair formula
• Echinacea purpurea 3x | Irritation reducer
• Hydrocotyle asiatica 3x | Irritation reducer

Uses

- relieves vaginal pain, itching, burning and discomfort

Warnings

For vaginal use only.

When using this product

- do not use tampons, douches or other vaginal products
- do not exceed the recommended dosage unless directed by a physician

Stop use and ask a doctor if

- condition worsens or does not improve within 7 days

PREGNANCY OR BREAST FEEDING

If pregnant or breast-feeding, ask a health care professional before use.

Keep out of reach of children. If swallowed, get medical help or contact a poison control center right away.

Directions

Insert 1 applicatorful (2.5cc) into the vagina at bedtime for 14 consecutive nights.

Afterwards apply 3 times a week or as needed. Wash applicator after use.

Other Information

- do not use if seal over tube opening has been punctured
- do not purchase if carton is open
- store at 20-25°C (68 to 77°F)
- keep out of direct sunlight

Inactive Ingredients

cetyl alcohol, cetyl palmitate, disodium EDTA, hypromellose, methylparaben, polysorbate 60, propylene glycol, silicon dioxide, stearyl alcohol, white petrolatum, water

Questions?

Call 1-800-956-2595 Monday thru Friday 8am - 5pm EST

Distributed by: Izun Pharmaceuticals Corp.
New York, NY 10022 USA

PRINCIPAL DISPLAY PANEL - 39.7 g Tube Carton

Herbal Formula
Natural BioActives
NDC 49589-115-60

Natural Vaginal Care

Vaginal Cream

Relieves Vaginal Pain, Itching,
Burning & Discomfort

- Fast Acting Relief
- Soothing Herbal Formula
- Package includes
  3 reusable applicators

NET WT
1.4 OZ
(39.7 g)

Homeopathic

izun
Pharmaceuticals